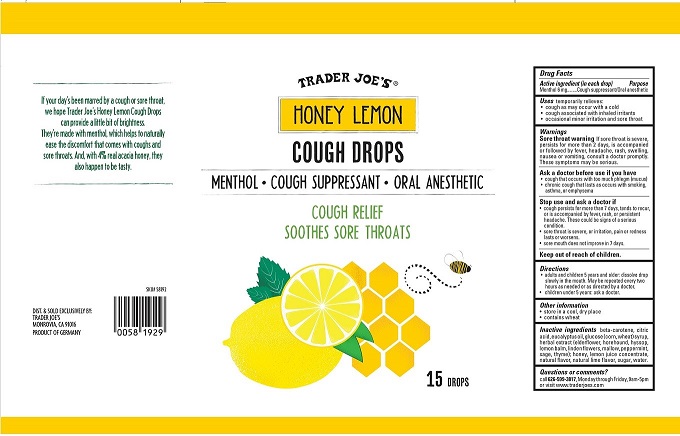 DRUG LABEL: Honey Lemon Cough Drops
NDC: 71270-581 | Form: LOZENGE
Manufacturer: Trader Joe's Company
Category: otc | Type: HUMAN OTC DRUG LABEL
Date: 20251031

ACTIVE INGREDIENTS: MENTHOL 6 mg/1 1
INACTIVE INGREDIENTS: SUCROSE; PEPPERMINT; TILIA CORDATA FLOWER; .BETA.-CAROTENE; WATER; CORN SYRUP; CITRIC ACID MONOHYDRATE; MELISSA OFFICINALIS; SAGE; EUCALYPTUS OIL; MALVA NEGLECTA WHOLE; HYSSOPUS OFFICINALIS FLOWERING TOP; HONEY; LEMON JUICE; THYME; SAMBUCUS NIGRA FLOWER; HOREHOUND

TRADER JOE'S HONEY LEMON COUGH DROPS

Drug Facts

Active ingredient (in each drop)

Menthol 6 mg

Purpose

Cough suppressant/Oral anesthetic

INDICATIONS AND USAGE

Usestemporarily relieves:

- cough as may occur with a cold
- cough associated with inhaled irritants
- occasional minor irritation and sore throat

Warnings

Sore throat warningIf sore throat is severe, persists for more than 2 days, is accompanied or followed by fever, headache, rash, swelling, nausea or vomiting, consult a doctor promptly. These symptoms may be serious.

Ask a doctor before use if you have

- cough that occurs with too much phlegm (mucus)
- chronic cough that lasts such as occurs with smoking, asthma, or emphysema

Stop use and ask a doctor if

- cough persists for more than 7 days, tends to recur, or is accompanied by fever, rash, or persistent headache. These could be signs of a serious condition.
- sore throat is severe, or irritation pain or redness lasts or worsens.
- sore mouth does not improve in 7 days.

Keep out of reach of children.

Directions

- adults and children 5 years and older: dissolve drop slowly in the mouth. May be repeated every two hours as needed or as directed by a doctor
- children under 5 years: ask a doctor

Other information

- store in a cool, dry place
- contains wheat

INACTIVE INGREDIENT

Inactive ingredientsbeta carotene, citric acid, eucalyptus oil, glucose (corn, wheat) syrup, herbal extract (elderflower, horehound, hyssop, lemon balm, linden flowers, mallow, peppermint, sage, thyme); honey, lemon juice concentrate, natural flavor, natural lime flavor, sugar, water.

If your day's been marred by a cough or sore throat, we hope Trader Joe's Honey Lemon Cough Drops can provide a little bit of brightness. They're made with menthol, which helps to naturally ease the discomfort that comes with coughs and sore throats. And, with 4% real acacia honey, they also happen to be tasty.

DIST. & SOLD EXCLUSIVELY BY:

TRADER JOE'S

MONROVIA, CA 91016

PRODUCT OF GERMANY

PACKAGE LABEL

TRADER JOE'S®

HONEY LEMON

COUGH DROPS

MENTHOL•COUGH SUPPRESSANT•ORAL ANESTHETIC

COUGH RELIEF

SOOTHES SORE THROATS

15 DROPS